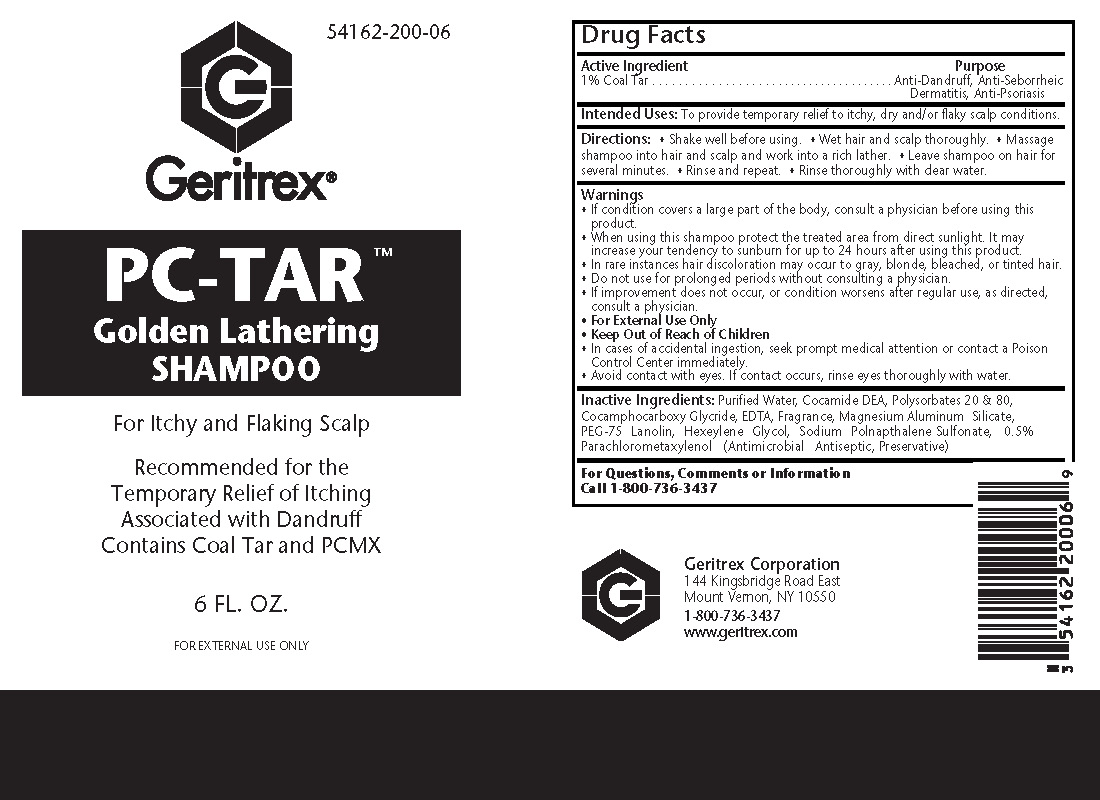 DRUG LABEL: PC-TAR
NDC: 54162-200 | Form: SHAMPOO
Manufacturer: Geritrex LLC
Category: otc | Type: HUMAN OTC DRUG LABEL
Date: 20160705

ACTIVE INGREDIENTS: COAL TAR 1.77441 g/177.441 mL
INACTIVE INGREDIENTS: WATER; COCAMIDE; POLYSORBATE 20; POLYSORBATE 80; EDETIC ACID; MAGNESIUM ALUMINUM SILICATE; PEG-75 LANOLIN; HEXYLENE GLYCOL; NAPHTHALENESULFONIC ACID (MIXED ISOMERS); CHLOROXYLENOL

PC-TAR

Purpose:

Anti-dandruff, anti-seborrheic dermatitis, anti-psoriasis

Intended Uses:

To provide temporary relief to itchy, dry, and/or flaky scalp conditions

Directions:

Shake well before using

Wet hair and scalp thoroughly

Massage shampoo into hair and scalp and work into a rich lather

Leave shampoo on hair for several minutes

Rinse and repeat

Rinse thoroughly with water

Warnings:

If condition covers a large part of the body, consult a physician before using this product
When using this shampoo protect the treated area from direct sunlight. It may increase your tendency to sunburn for up to 24 hours after using this product.
In rare instances hair discoloration may occur to gray, blonde, bleached, or tinted hair.
Do not use for prolonged periods without consulting a physician.
If improvement does not occur, or condition worsens after regular use or as directed, consult a physician
FOR EXTERNAL USE ONLY

WARNINGS AND PRECAUTIONS

In case of accidental ingestion, seek prompt medical attention or contact a Poison Control Center immediately.
Avoid contact with the eyes. If contact occurs, rinse thoroughly with water.

Inactive Ingredients:

Purified water, Cocamide DEA, Polysorbate 20 & 80, Cocamphocarboxy Glyceride, EDTA, Fragrance, Magnesium Aluminum Silicate, PEG-75 Lanolin, Hexeylene Glycol, Sodium Polnapthalene Sulfonate, 0.5% Parachlorometaxylenol (antimicrobial preservative)